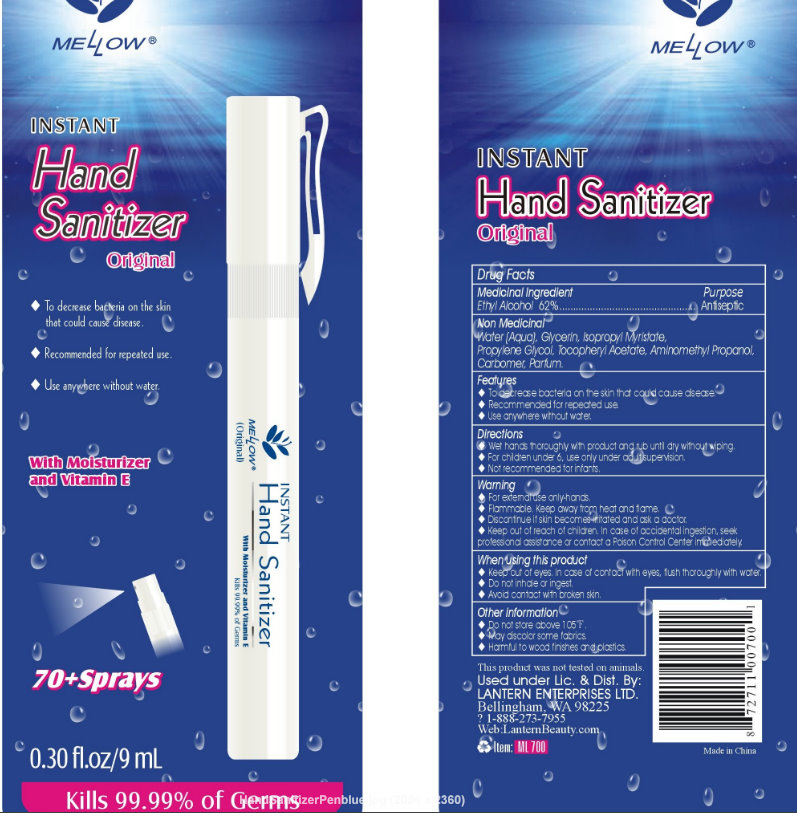 DRUG LABEL: Instant Hand Sanitizer Original With Moisturizer and Vitamin E
NDC: 50154-1050 | Form: SPRAY
Manufacturer: Lantern Enterprises Ltd
Category: otc | Type: HUMAN OTC DRUG LABEL
Date: 20100528

ACTIVE INGREDIENTS: ALCOHOL 62 mL/100 mL
INACTIVE INGREDIENTS: WATER; GLYCERIN; ISOPROPYL MYRISTATE; PROPYLENE GLYCOL

Instant Hand Sanitizer Original With Moisturizer and Vitamin E

Medicinal Ingredient Purpose
Ethyl Alcohol 62%........................................Antiseptic

INACTIVE INGREDIENT

Non Medicinal
Water (Aqua), Glycerin, Isopropyl Myristate, Propylene Glycol, Tocopheryl Acetate, Aminomethyl Propanol, Carbomer, Parfum.

DESCRIPTION

Features

To decrease bacteria on the skin that could cause disease
Recommended for repeated use.
Use anywhere without water.

Directions

Wet hands thoroughly with product and rub until dry without wiping.
For children under 6, use only under adult supervision.
Not recommended for infants.

Warning

For external use only-hands.
May discolor some fabrics.
Harmful to wood finishes and plastics.

STORAGE AND HANDLING

Flammable, keep away from heat and flame.
Do not store above 105 degree Fahrenheit.

ASK DOCTOR

Discontinue if skin becomes irritated and ask a doctor.

Keep out of reach of children. In case of accidental ingestion, seek professional assistance or contact a Poison Control Center immediately.

WHEN USING

Keep out of eyes. In case of contact with eyes, flush thoroughly with water.
Do not inhale or ingest.
Avoid contact with broken skin.

DESCRIPTION

This product was not tested on animals.

Use under Lic. and Dist. By:
LANTERN ENTERPRISES LTD.
Bellingham, WA 98225

? 1-888-273-7955

Web: LanternBeauty.com

Item ML 700

Made in China

PACKAGE LABEL

MELLOW

INSTANT Hand Sanitizer Original

To decrease bacteria on the skin that could cause disease.
Recommended for repeated use.
Use anywhere without water.

With Moisturizer and Vitamin E

70+ Sprays

0.30 fl.oz/9 mL

Kills 99.99% of Germs

INSTANT Hand Sanitizer With Moisturizer and Vitamin E
Kills 99.99% Germs

MELLOW (Original)